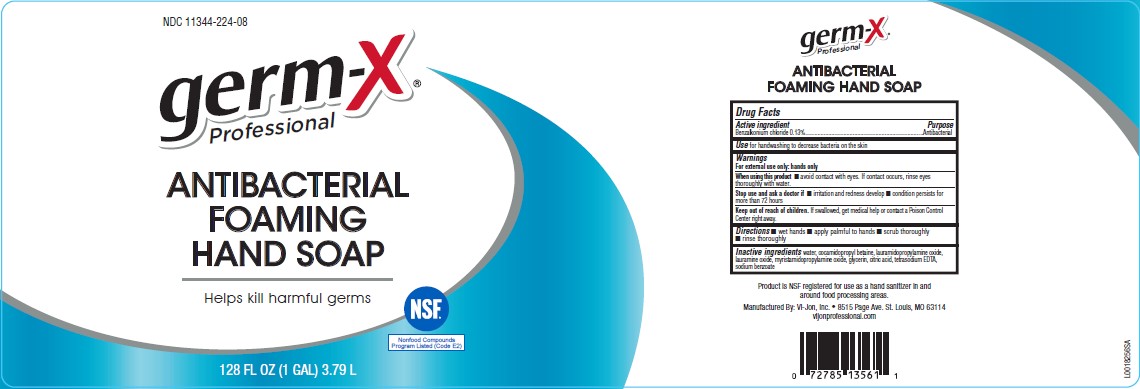 DRUG LABEL: Foaming Hand
NDC: 11344-224 | Form: LOTION
Manufacturer: Consumer Product Partners, LLC
Category: otc | Type: HUMAN OTC DRUG LABEL
Date: 20250414

ACTIVE INGREDIENTS: BENZALKONIUM CHLORIDE 1.3 mg/1 mL
INACTIVE INGREDIENTS: WATER; COCAMIDOPROPYL BETAINE; LAURAMIDOPROPYLAMINE OXIDE; LAURAMINE OXIDE; MYRISTAMIDOPROPYLAMINE OXIDE; GLYCERIN; CITRIC ACID MONOHYDRATE; EDETATE SODIUM; SODIUM BENZOATE

Germ-X 224.000/224AA
Antibacterial Foaming Hand Soap

Claims

germ-X

Professional

ANTIBACTERIAL

FOAMING HAND SOAP

Active ingredient

Benzalkonium chloride 0.13%

Purpose

Antibacterial

Use

for handwashing to decrease bacteria on the skin

Warnings

For external use only: hands only

When using this product

- avoid contact with eyes. If contact occurs, rinse eyes thoroughly with water.

Stop use and ask a doctor if

- irritation and redness develop
- condition persists for more than 72 hours

Keep out of reach of children.

If swallowed, get medical help or contact a Poison Control Center right away.

Directions

- wet hands
- apply palmful to hands
- scrub thoroughly
- rinse thoroughly

Inactive ingredients

water, cocamidopropyl betaine, lauramidopropylamine oxide, lauramine oxide, myristamidopropylamine oxide, glycerin, citric acid, tetrasodium EDTA, sodium benzoate

Claims

Product is NSF registered for us as a hand sanitizer in and around food processing areas.

Adverse event

Manufactured By: Vi-Jon, Inc. 8515 Page Ave. St. Louis, Mo 63114

vijonprofessional.com

Adverse event

NDC 11344-224-08

germ-X®

Professional

ANTIBACTERIAL

FOAMING

HAND SOAP

Helps kill harmful germs

128 FL OZ (1 GAL) 3.79 L